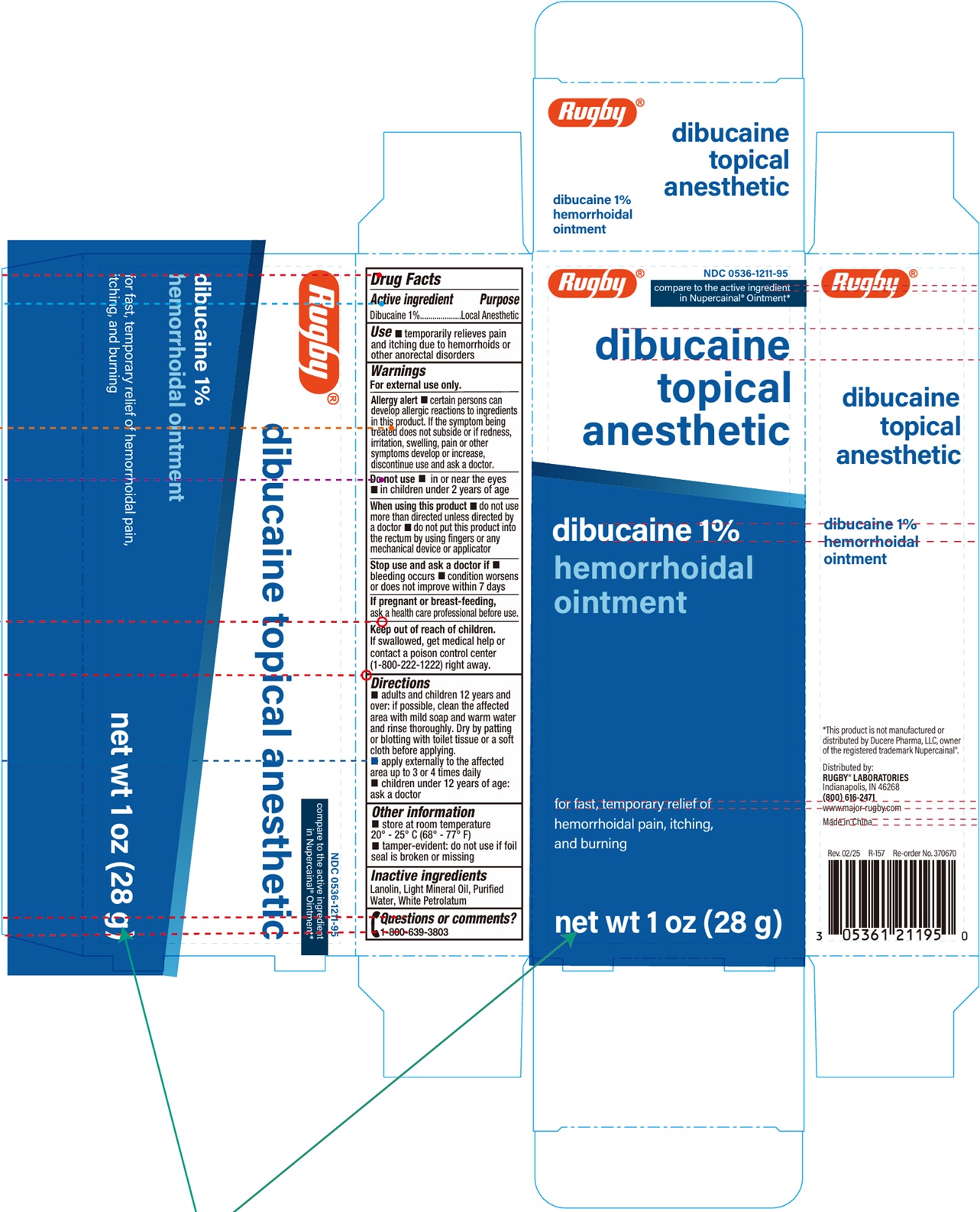 DRUG LABEL: Dibucaine Topical Anesthetic 1% Hemorrhoidal
NDC: 0536-1211 | Form: OINTMENT
Manufacturer: Rugby Laboratories Inc.
Category: otc | Type: HUMAN OTC DRUG LABEL
Date: 20250529

ACTIVE INGREDIENTS: DIBUCAINE 10 mg/1 g
INACTIVE INGREDIENTS: LANOLIN; LIGHT MINERAL OIL; WATER; PETROLATUM

Dibucaine Topical Anesthetic 1% Hemorrhoidal Ointment

Active ingredient

Dibucaine 1%

Purpose

Local Anesthetic

Use

- temporarily relieves pain and itching due to hemorrhoids and other anorectal disorders

Warnings

For external use only.

Allergy Alert

- Certain persons can develop allergic reactions to ingredients in this product. If the symptoms being treated does not subside or if redness, irritaion, swelling, bleeding or other symptoms develop or increase, discontinue use and ask a doctor.

Do not use

- in or near the eyes
- in children under 2 years of age

When using this product

- do not use more than directed unless directed by a doctor.
- do not put this product into the rectum by using fingers or any mechanical device or applicator

Stop use and ask a doctor if

- bleeding occurs
- condition worsens or does not improve within 7 days

If pregnant or breast-feeding

ask a health care professional before use.

Keep out of reach of children.

If swallowed, get medical help or contact a poison control center (1-800-222-1222) right away.

Directions

- adults and children 12 years and over: If possible, clean the affected area with mild soap and warm water and rinse thoroughly. Dry by patting or blotting with toilet tissue or a soft cloth before applying.
- apply externally to the affected area up to 3 to 4 times daily.
- children under 12 years of age: ask a doctor

Other information

- Store at 20o-25o C (68o-77o F)
- tamper-evident: do not use if foil seal is broken or missing

undefined

Lanolin, Light Mineral Oil, Purified Water, White Petrolatum

Questions or comments?

call 1-800-639-3803